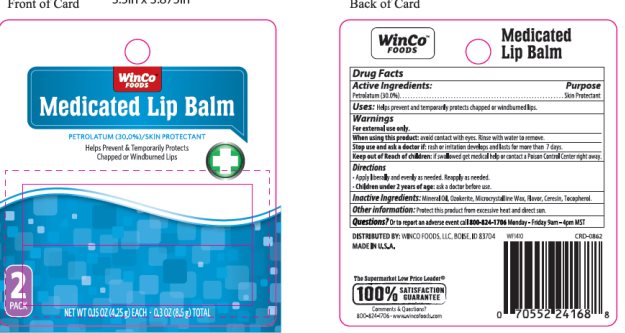 DRUG LABEL: Winco Medicated Lip Balm
NDC: 67091-251 | Form: STICK
Manufacturer: Winco
Category: otc | Type: HUMAN OTC DRUG LABEL
Date: 20250307

ACTIVE INGREDIENTS: PETROLATUM 30.0 mg/1 g
INACTIVE INGREDIENTS: LIGHT MINERAL OIL 39 mg/1 g; MICROCRYSTALLINE WAX 3.00 mg/1 g; CERESIN 24 mg/1 g

Drug Facts

Active ingredient

Petrolatum

Purpose

Skin Protectant

Keep Out of Reach of Children

If swallowed get medical help or contact a Poison Control Center right away.

Uses

Helps prevent and temporarily protects dry, chapped or windburned lips.

Warnings

For external use only

Stop use and ask a doctor: If rash or irritation develops and lasts for more than 7 days.

When using this product: avoid contact with eyes. Rinse with water to remove.

Keep out of reach of children: If swallowed get medical help or contact a Poison Control Center right away.

Directions

Apply liberally and evenly as needed. Reapply as needed.

Children under 6 months of age: Ask a doctor before use.

Inactive Ingredients

Mineral Oil, Ozokerite, Microcrystalline Wax, Flavor, Cereson, Tocopherol.